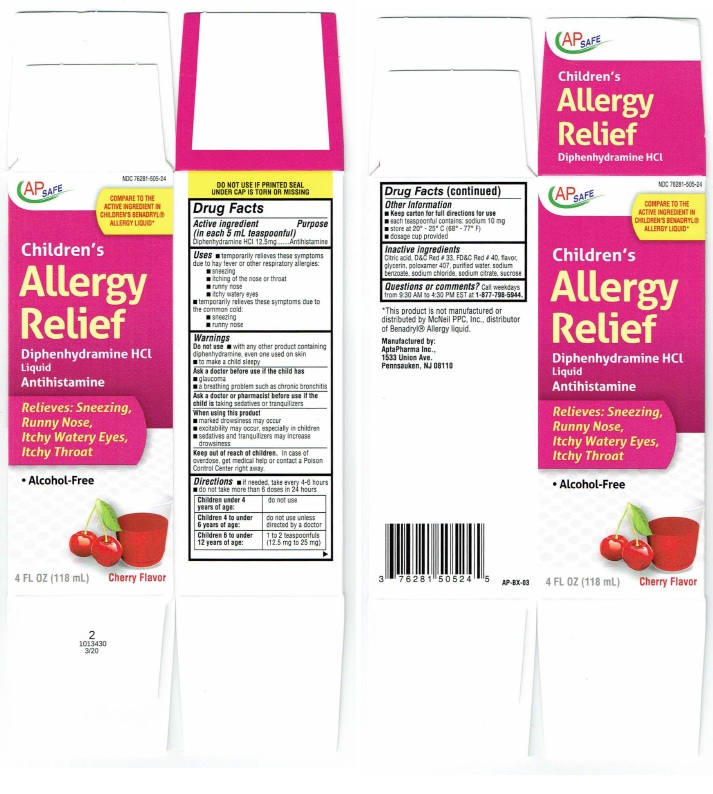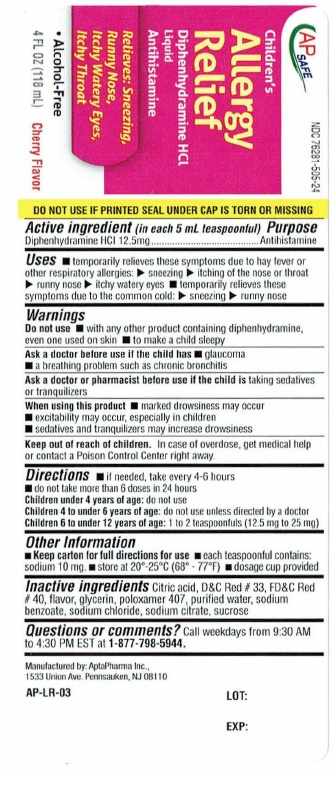 DRUG LABEL: Childrens Allergy
NDC: 76281-505 | Form: LIQUID
Manufacturer: AptaPharma Inc.
Category: otc | Type: HUMAN OTC DRUG LABEL
Date: 20251226

ACTIVE INGREDIENTS: DIPHENHYDRAMINE HYDROCHLORIDE 12.5 mg/5 mL
INACTIVE INGREDIENTS: CITRIC ACID MONOHYDRATE; D&C RED NO. 33; FD&C RED NO. 40; GLYCERIN; POLOXAMER 407; WATER; SODIUM BENZOATE; SODIUM CHLORIDE; SODIUM CITRATE; SUCROSE

Drug Facts

Active ingredient
(in each 5 mL teaspoon)

Diphenhydramine HCL 12.5 mg

Purpose

Antihistamine

Uses
■ Temporarily relieves these symptoms
due to hay fever or other respiratory allergies:
■ sneezing
■ itching of the nose or throat
■ runny nose
■ itchy watery eyes
■ temporarily relieves these symptoms due to
the common cold:
■ sneezing
■ runny nose

Warnings
Do not use ■ with any other product containing
diphenhydramine, even one used on skin
■ to make a child sleepy

Ask a doctor before use if the child has
■ glaucoma
■ abreathing problem such as chronic bronchitis

Ask a doctor or pharmacist before use if the
child is taking sedatives or tranquilizers

When using this product

■ marked drowsiness may occur
■ excitability may occur, especially in children
■ sedatives and tranquilizers may increase
drowsiness

Keep out of reach of children.In case of
overdose, get medical help or contact a Poison
Control Center right away.

DOSAGE AND ADMINISTRATION

Directions■ if needed, take every 4-6 hours■ do not take more than 6 doses in 24 hours

Children under 4 years of age: | do not use
Children 4 to under 6 years of age: | do not use unless directed by a doctor
Children 6 to under 12 years of age: | 1 to 2 teaspoonfuls (12.5 mg to 25 mg)

Other Information

■ Keep carton for full directions for use
■ each teaspoonful contains: sodium 10 mg
■ store at 20° - 25° C(68° - 77° F)
■ dosage cup provided

Inactive ingredients
Citric acid, D&C Red # 33, FD&C Red # 40, flavor,
glycerin, poloxamer 407, purified water, sodium
benzoate, sodium chloride, sodium citrate, sucrose

Questions or comments?Call weekdays
from 9:30 AM to 4:30 PM EST at 1-877-798-5944.

Product Label

AP SAFE NDC 72681-505-24

COMPARE TO THE
ACTIVE INGREDIENT IN
CHILDREN'S BENADRYL®
ALLERGY LIQUID*

Children's
Allergy
Relief

DIPHENHYDRAMINE HCl
Liquid
Antihistamine

Relieves: Sneezing,
Runny Nose,
Itchy Watery Eyes,
Itchy Throat

• Alcohol-Free

4 FL OZ (118 mL) Cherry Flavor

DO NOT USE IF PRINTED SEAL
UNDER CAP IS TORN OR MISSING

2
1013430
3/20

*This product is not manufactured or
distributed by McNeil PPC, Inc., distributor
of Benadryl®Allergy liquid.

Manufactured by:
AptaPharma Inc.,
1533 Union Ave.
Pennsauken, NJ 08110

AP-BX-03

Carton

Bottle

res